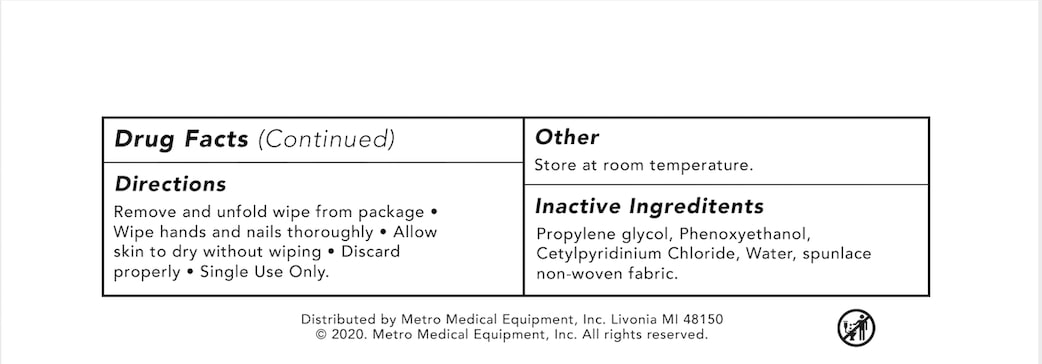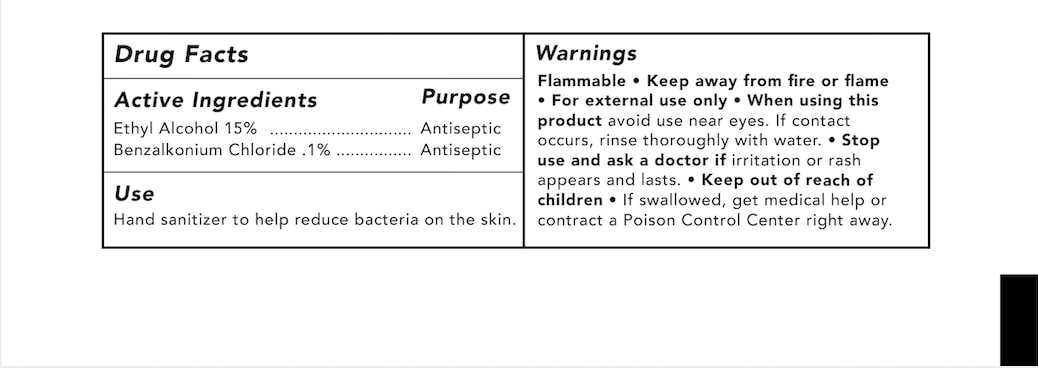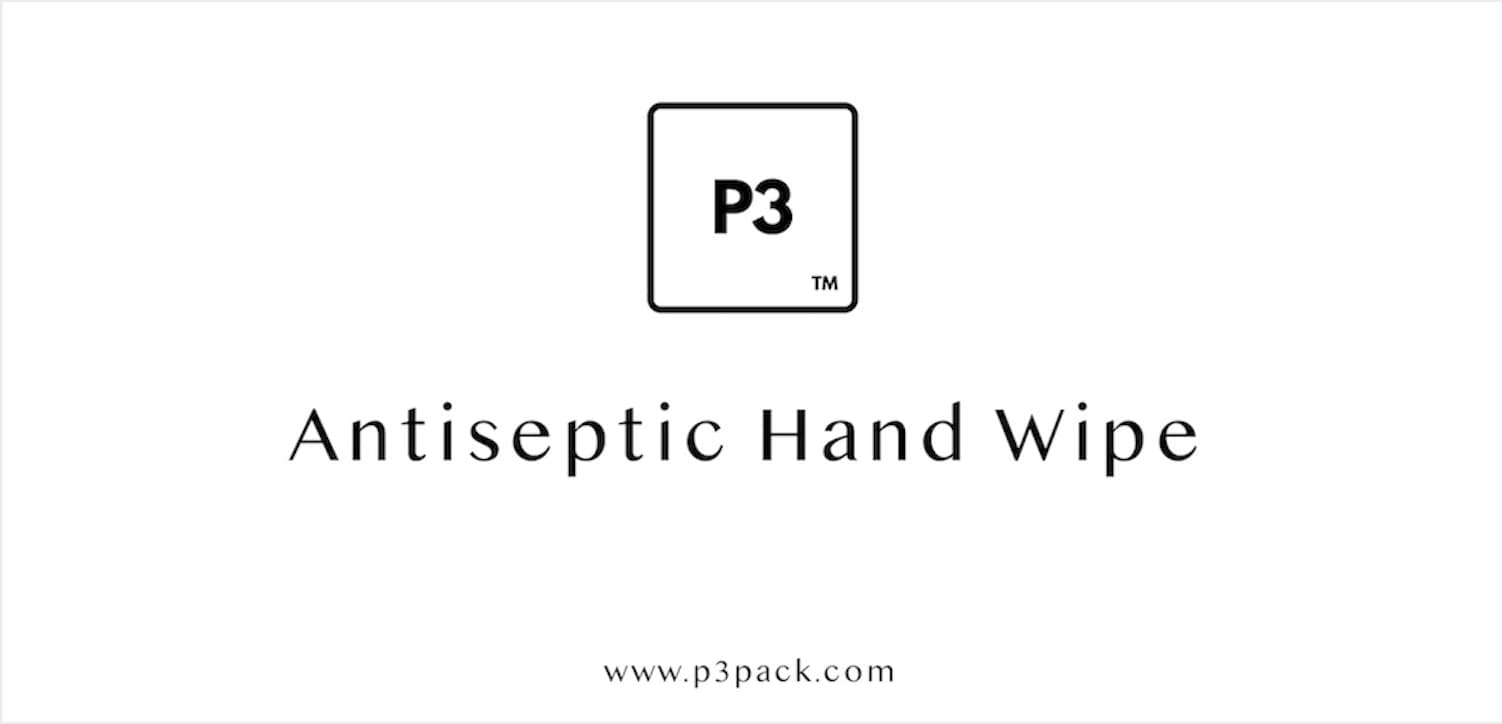 DRUG LABEL: Antiseptic Hand Wipe
NDC: 90024-001 | Form: CLOTH
Manufacturer: Metro Medical Equipment Mfg. Inc
Category: otc | Type: HUMAN OTC DRUG LABEL
Date: 20200827

ACTIVE INGREDIENTS: BENZALKONIUM CHLORIDE 0.1 g/100 g; ALCOHOL 15 g/100 g
INACTIVE INGREDIENTS: PHENOXYETHANOL; CETYLPYRIDINIUM CHLORIDE

DOSAGE AND ADMINISTRATION

Remove and unfold wipe from package

Wipe hands and nails thoroughly

Allow sking to dry without wiping

Discard Properly

Single Use Only

ACTIVE INGREDIENT

Ethyl Alcohol 15%

Benzalkonium Chloride .1%

INDICATIONS AND USAGE

Hand sanitizer to help reduce bacteria on the skin.

Keep out of reach of children.

PURPOSE

Antiseptic

INTENDED USE OF THE DEVICE

Hand sanitizer to help reduce bacteria on the skin.

WARNINGS

Flammable

Keep away from fire or flame

For external use only

When using this product aboid use near eyes

If contact occurs, rinse thoroughly with water

Stop use and ask a doctor if irritation or rash appears and lasts

Keep out of reach of children

If swallowed, get medical help or contact a Poison Control Center right away

Directions

Remove and unfold wipe from package

Wipe hands and nails thoroughly

Allow skin to dry without wiping

Discard properly

Single Use Only

Other

Store at room temperature

INACTIVE INGREDIENT

Propylene glycol

Phenoxyethanol

Cetylpyridinium Chloride

Water

spunlace non-woven fabric